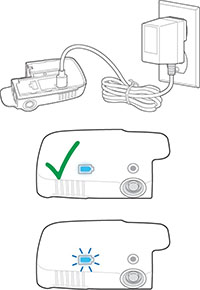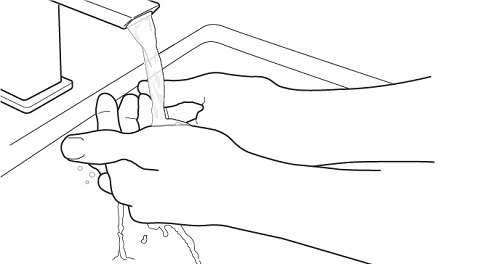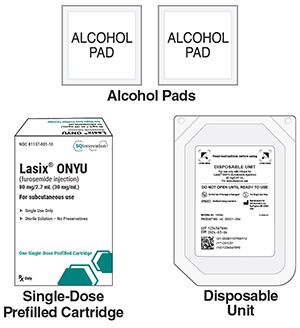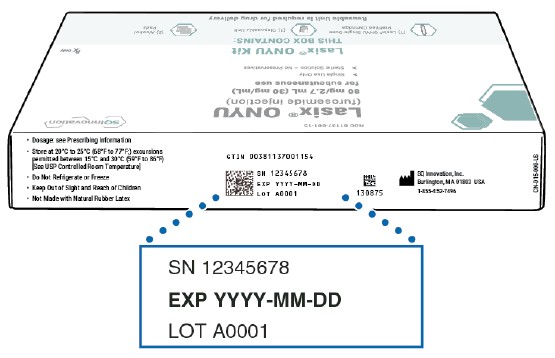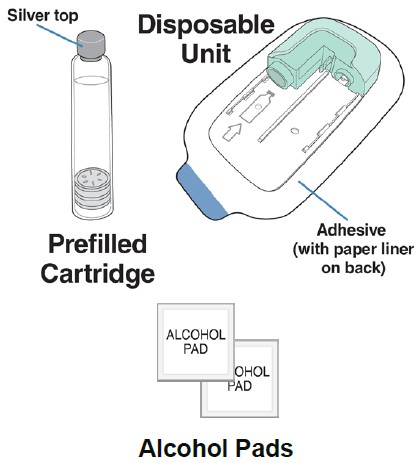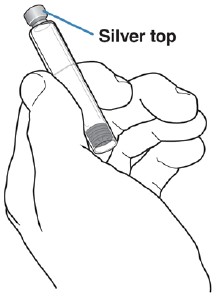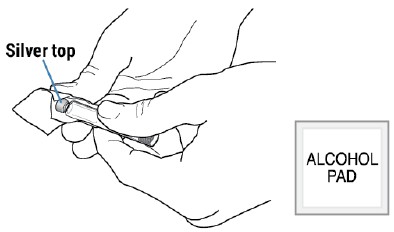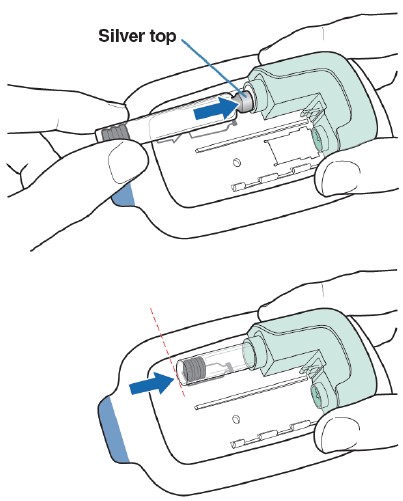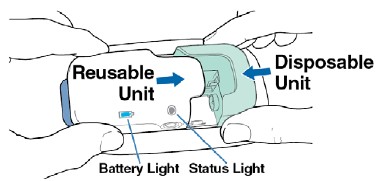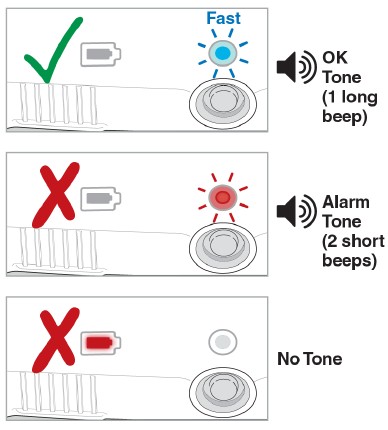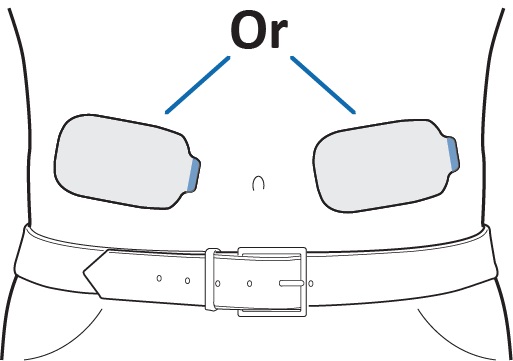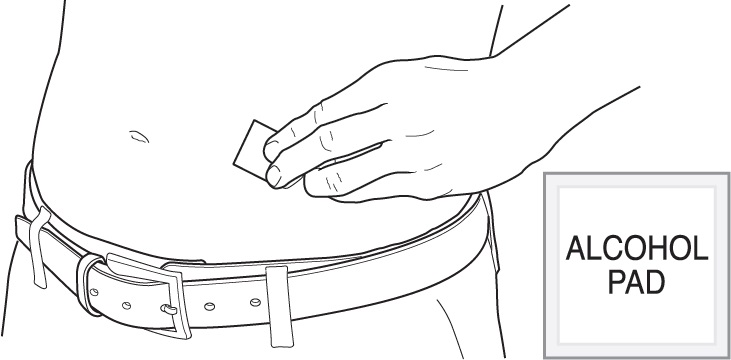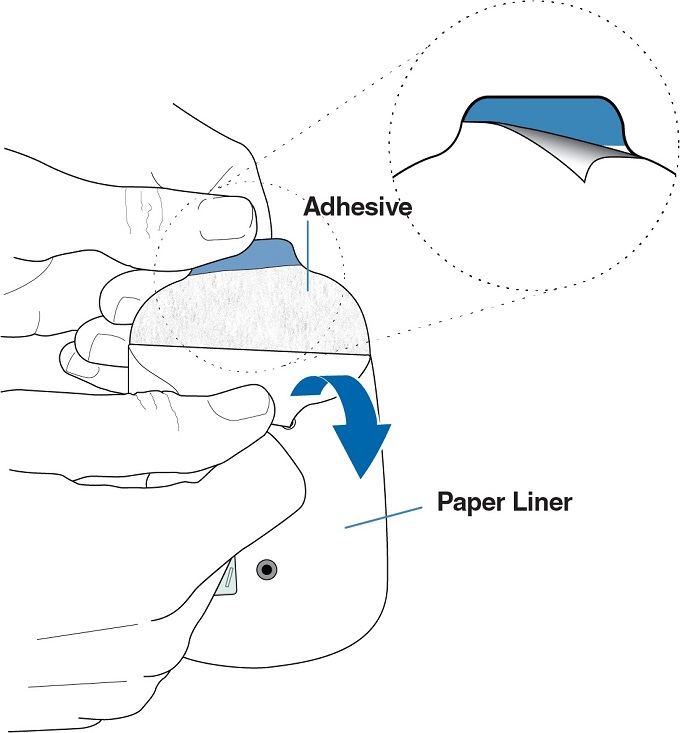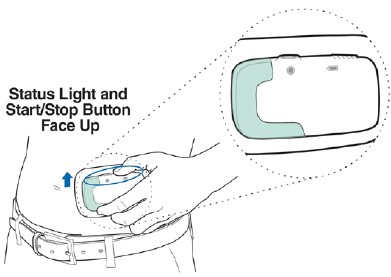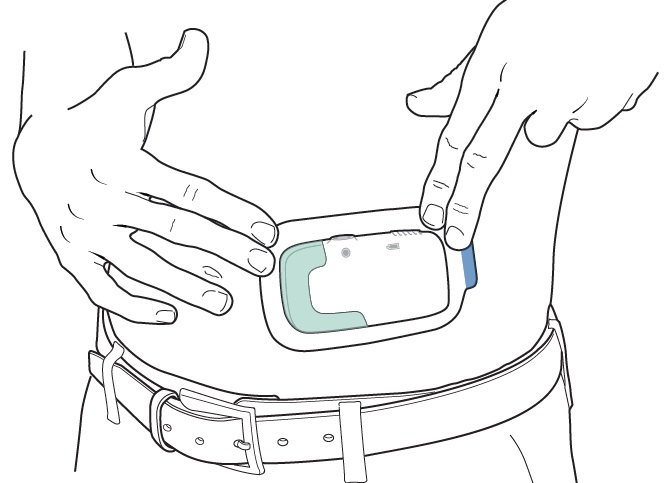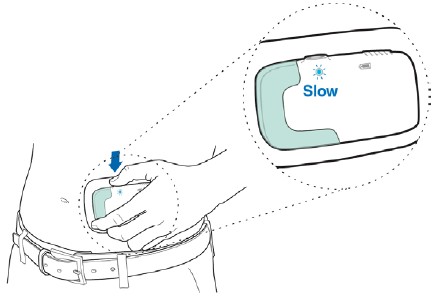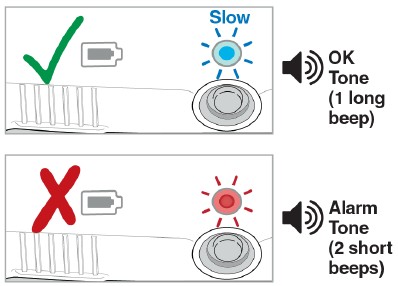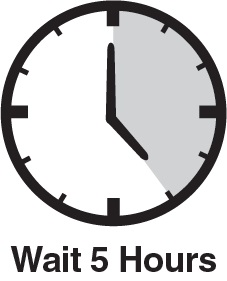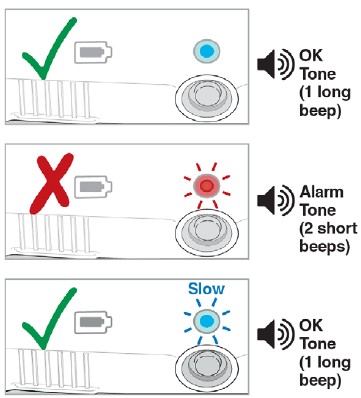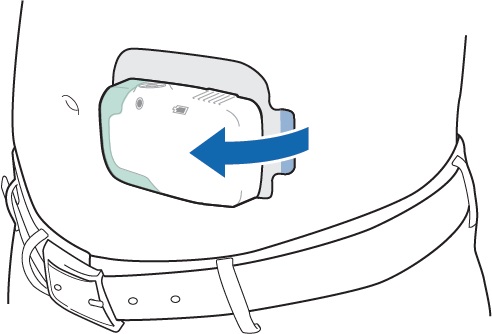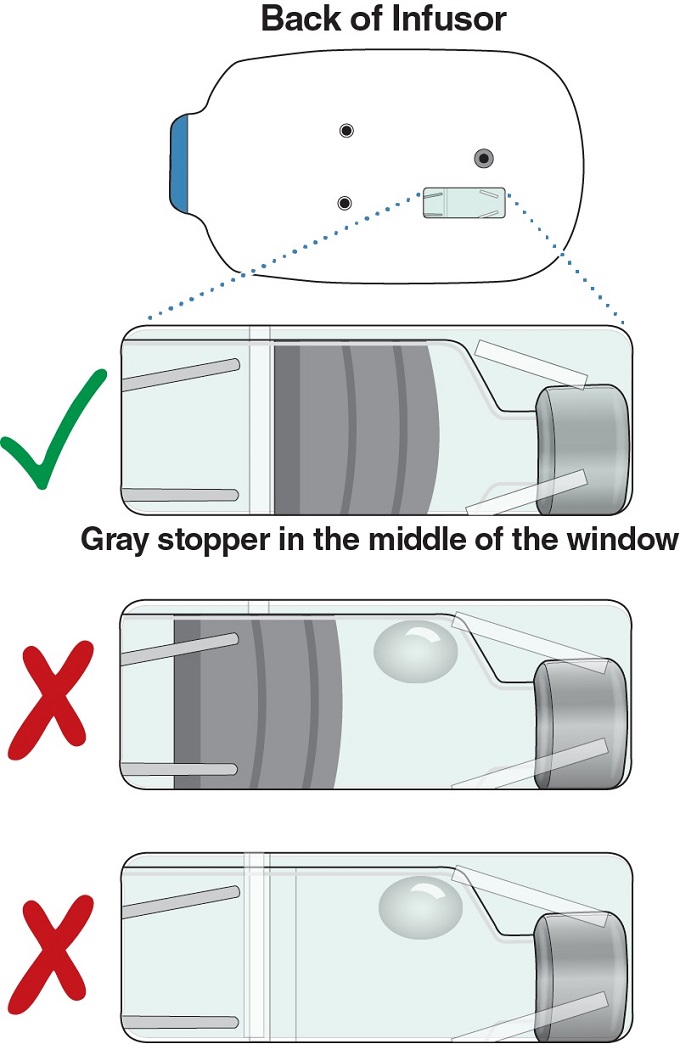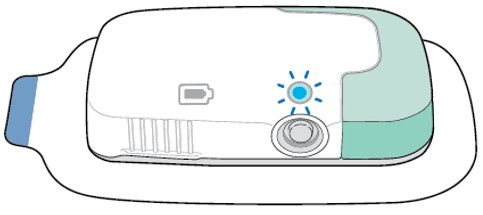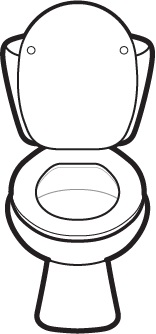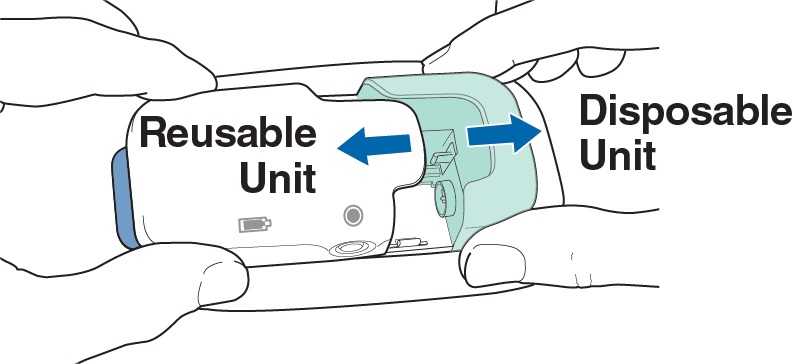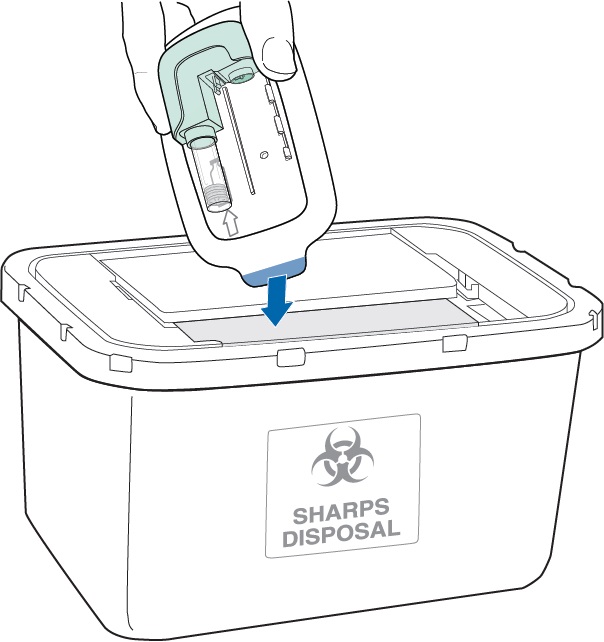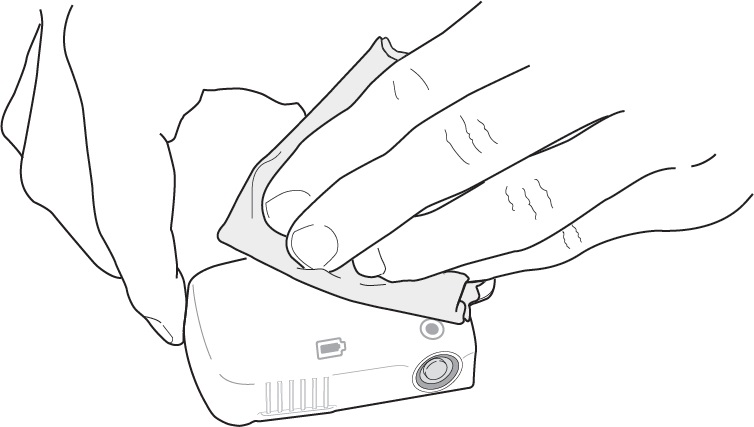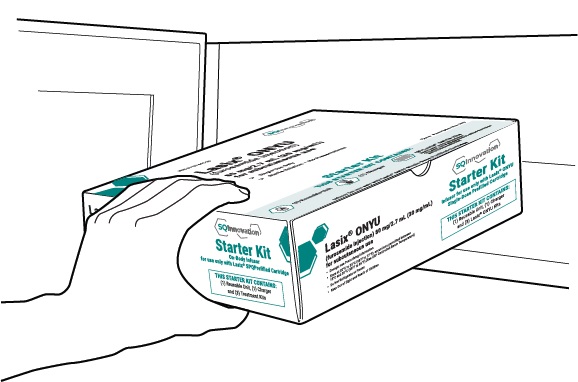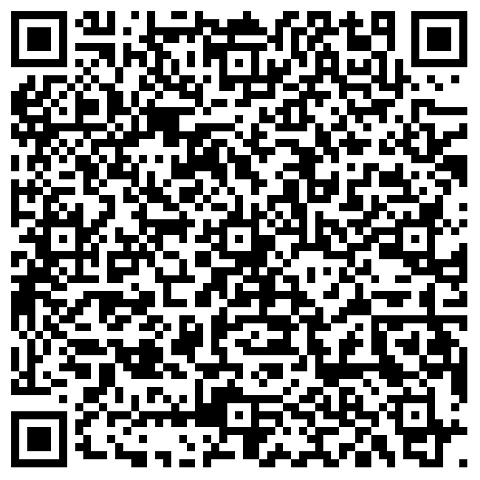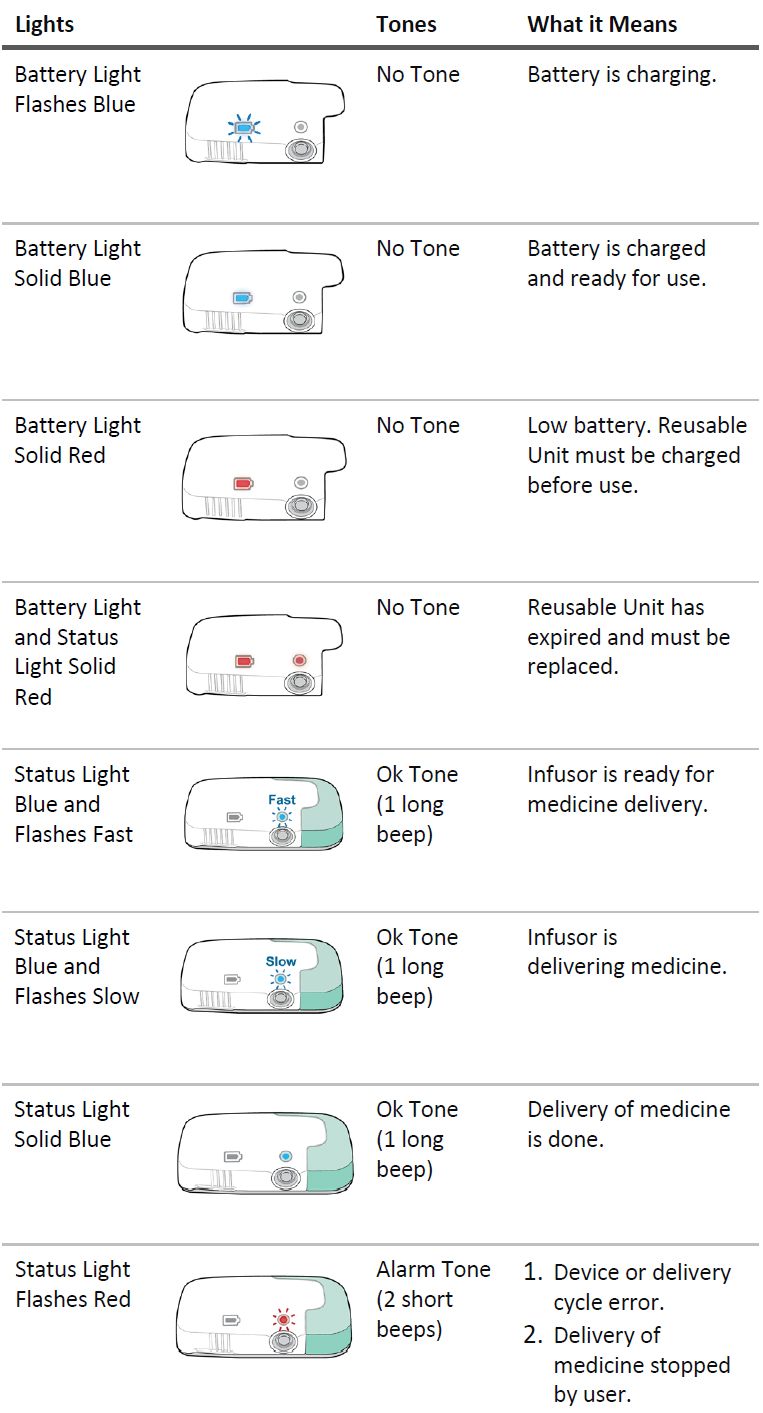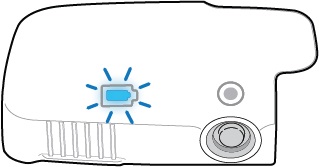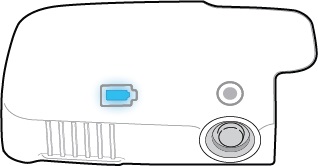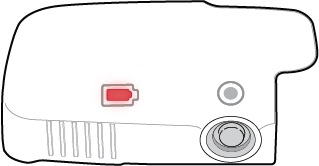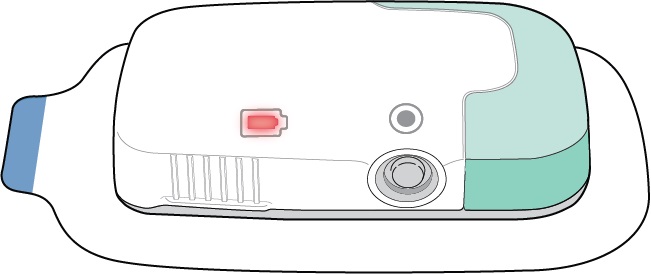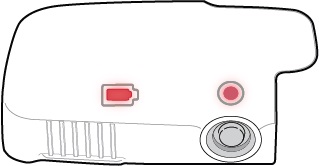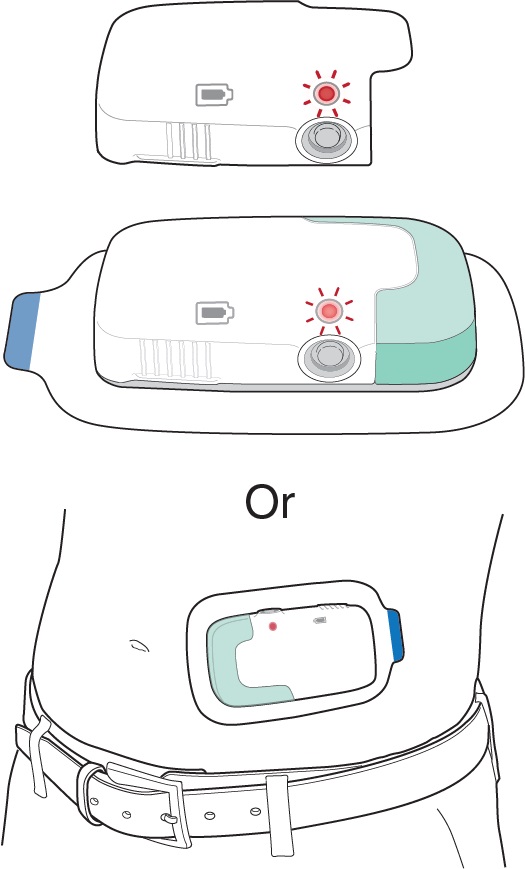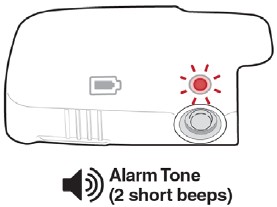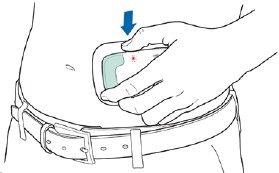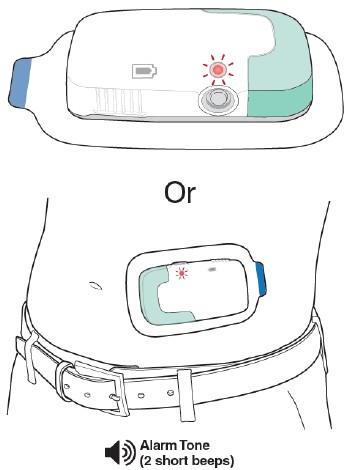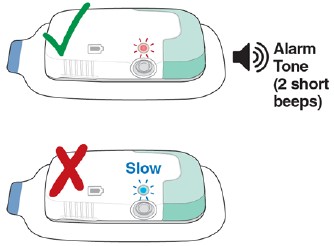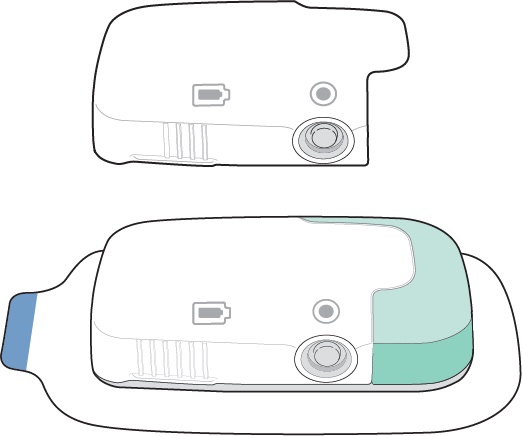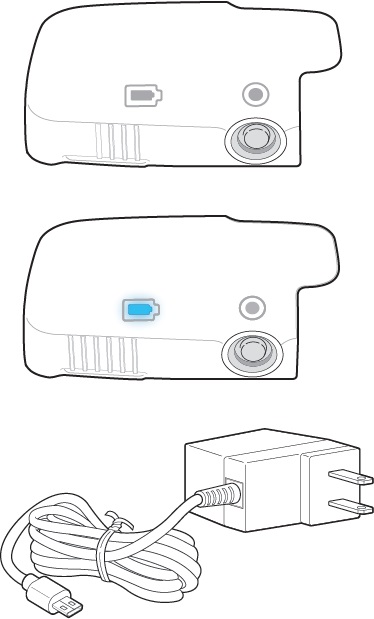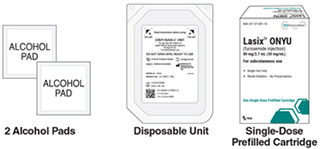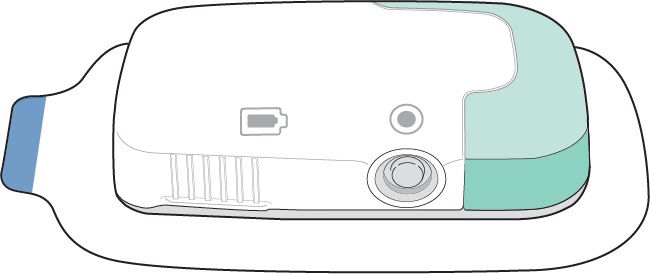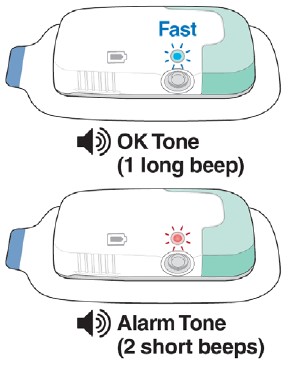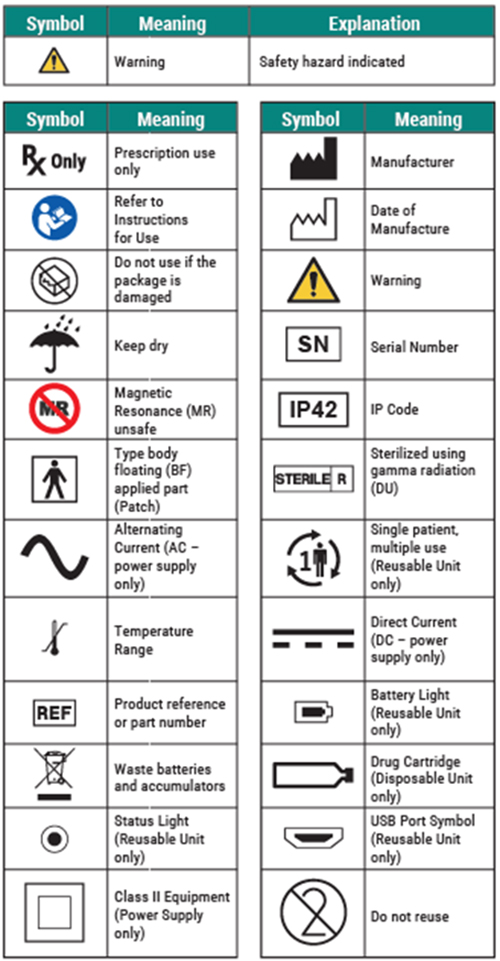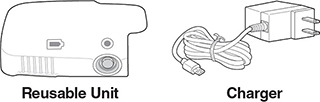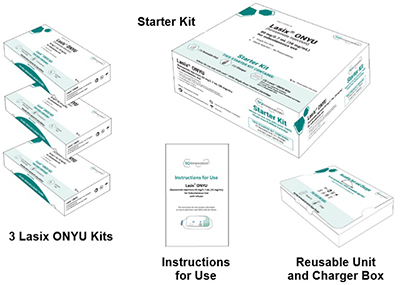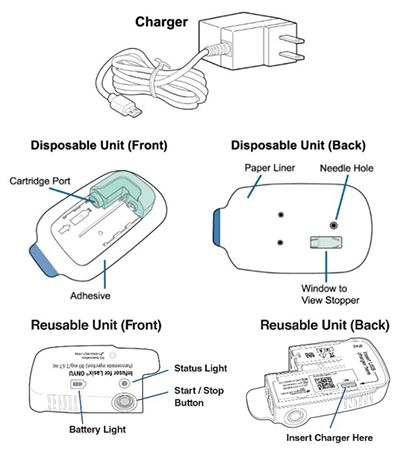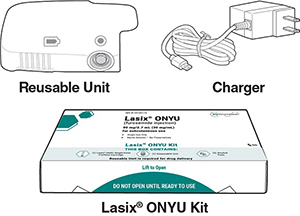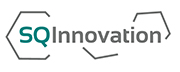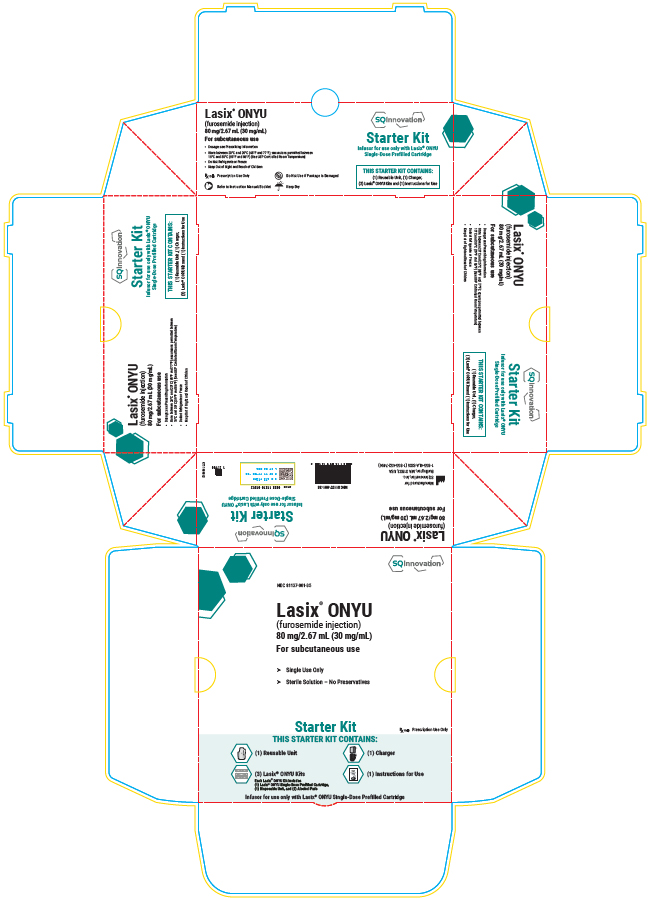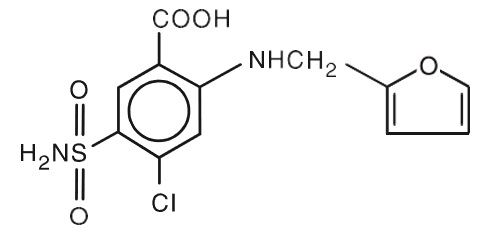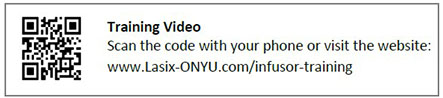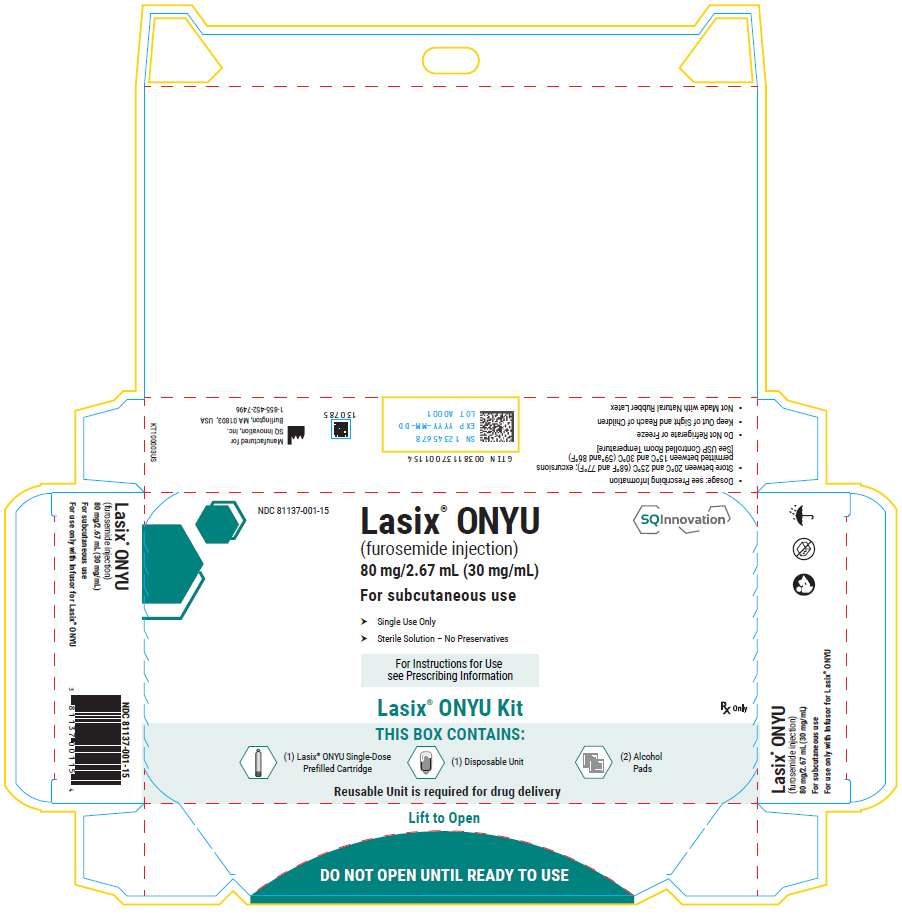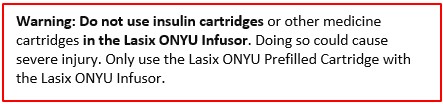 DRUG LABEL: LASIX ONYU
NDC: 81137-001 | Form: INJECTION
Manufacturer: SQ Innovation, Inc.
Category: prescription | Type: HUMAN PRESCRIPTION DRUG LABEL
Date: 20251114

ACTIVE INGREDIENTS: FUROSEMIDE 30 mg/1 mL
INACTIVE INGREDIENTS: HYDROCHLORIC ACID; SODIUM HYDROXIDE; BETADEX SULFOBUTYL ETHER SODIUM 300 mg/1 mL; TROMETHAMINE 3 mg/1 mL; WATER

HIGHLIGHTS OF PRESCRIBING INFORMATION

These highlights do not include all the information needed to use Lasix® ONYU safely and effectively. See full prescribing information for Lasix® ONYU. Lasix® ONYU (furosemide injection), for subcutaneous use
Initial U.S. Approval: 1968

1 INDICATIONS AND USAGE

Lasix ONYU is a loop diuretic indicated for the treatment of edema in adult patients with chronic heart failure. (1.1)

2 DOSAGE AND ADMINISTRATION

- The Infusor is pre-programmed to deliver 30 mg of Lasix ONYU over the first hour then 12.5 mg per hour for the subsequent 4 hours. (2.1)
- Lasix ONYU is not for chronic use and should be replaced with oral diuretics as soon as practical. (2.1)
- See Full Prescribing Information for important administration instructions. (2.2)

3 DOSAGE FORMS AND STRENGTHS

Injection: 80 mg per 2.67 mL in a single-dose prefilled cartridge co-packaged with a single-use Disposable Unit of the Infusor. (3)

4 CONTRAINDICATIONS

- Anuria. (4)
- Hypersensitivity to furosemide or medical adhesives. (4)

5 WARNINGS AND PRECAUTIONS

- Fluid, Electrolyte, and Metabolic Abnormalities: Monitor serum electrolytes, CO2, BUN, creatinine, glucose, and uric acid. (5.1)
- Worsening Renal Function: Monitor for dehydration and azotemia. (5.2)
- Ototoxicity: Avoid higher than recommended doses. (5.3, 7.1)
- Acute Urinary Retention: Monitor patients with symptoms of urinary retention. (5.4)
- Incomplete Dosing: Fluid contact and certain patient movements during treatment may cause the On-body Infusor to prematurely terminate infusion. Ensure patients can detect and respond to alarms. (5.5)

6 ADVERSE REACTIONS

The most common adverse reactions during treatment with the Lasix ONYU Infusor were administration site and skin reactions: erythema, bruising, edema, and infusion site pain. (6)

To report SUSPECTED ADVERSE REACTIONS, contact SQ Innovation, at 1-855-452-7496 or FDA at 1-800-FDA-1088 or www.fda.gov/medwatch.

7 DRUG INTERACTIONS

- Aminoglycoside antibiotics: Increased potential ototoxicity of the antibiotics. Avoid combination. (7.1)
- Ethacrynic acid: Risk of ototoxicity. Avoid combination. (7.1)
- Salicylates: Risk of salicylate toxicity. (7.1)
- Cisplatin and nephrotoxic drugs: Risk of ototoxicity and nephrotoxicity. (7.1)
- Lithium: Risk of lithium toxicity. (7.1)
- Renin-angiotensin inhibitors: Increased risk of hypotension and renal failure. (7.1)
- Adrenergic blocking drugs: Risk of potentiation. (7.1)
- Drugs undergoing renal tubular secretion: Risk of toxicity potentiation. (7.1)

FULL PRESCRIBING INFORMATION

1 INDICATIONS AND USAGE

1.1 Congestion

Lasix ONYU is indicated for the treatment of edema in adult patients with chronic heart failure.

2 DOSAGE AND ADMINISTRATION

2.1 Dosage

The Infusor with single-dose prefilled cartridge delivers 30 mg of Lasix ONYU over the first hour followed by 12.5 mg per hour for the subsequent 4 hours [see Clinical Pharmacology (12)]. Administer Lasix ONYU once or twice daily as needed for edema. Lasix ONYU is not for chronic use and should be replaced with oral diuretics as soon as practical.

2.2 Important Administration Instructions

Lasix ONYU is intended for use in a setting where the patient can limit their activity for the duration of administration [see Warnings and Precautions (5.5)].

The Infusor for Lasix ONYU is not compatible with use in an MRI setting.

Inspect Lasix ONYU prefilled cartridge prior to administration. Lasix ONYU is a clear to slightly yellow solution. Do not use Lasix ONYU if solution is discolored or cloudy [see Description (11)] .

Refer to the Instructions for Use for additional information.

Push the Lasix ONYU prefilled cartridge into Disposable Unit. Slide the Reusable Unit and Disposable Unit together until the Status Light on the Reusable Unit turns on. The Infusor will remain ready to start infusion for 7 hours.

Peel away the paper liner on the Infusor and apply onto a clean, dry area of the abdomen between the top of the beltline and the bottom of the ribcage that is not tender, bruised, red, or indurated. Make sure the Status Lights and the Start/Stop Button are facing up in a horizontal position.

Start the injection by firmly pressing and holding the Start/Stop Button until you hear the motor and see the blue Status Light change to flashing slowly.

Do not remove until the injection is complete which is signaled by the solid blue Status Light and the OK tone (one long beep).

Rotate the site of each subcutaneous administration.

3 DOSAGE FORMS AND STRENGTHS

Injection: 80 mg per 2.67 mL as a clear to slightly yellow solution in a single-dose prefilled cartridge co-packaged with a single-use Disposable Unit of the Infusor.

4 CONTRAINDICATIONS

- Lasix ONYU is contraindicated in patients with anuria.
- Lasix ONYU is contraindicated in patients with a history of hypersensitivity to furosemide, any component of the Lasix ONYU formulation, or medical adhesives.

5 WARNINGS AND PRECAUTIONS

5.1 Fluid, Electrolyte, and Metabolic Abnormalities

Furosemide may cause fluid, electrolyte, and metabolic abnormalities such as hypovolemia, hypokalemia, azotemia, hyponatremia, hypochloremic alkalosis, hypomagnesemia, hypocalcemia, hyperglycemia, or hyperuricemia, particularly in patients receiving higher doses, patients with inadequate oral electrolyte intake, and in elderly patients. Excessive diuresis may cause dehydration and blood volume reduction with circulatory collapse and possible vascular thrombosis and embolism, particularly in elderly patients. Serum electrolytes, CO2, BUN, creatinine, glucose, and uric acid should be monitored frequently during furosemide therapy.

5.2 Worsening Renal Function

Furosemide can cause dehydration and azotemia. If increasing azotemia and oliguria occur during treatment of severe progressive renal disease, discontinue furosemide [see Clinical Pharmacology (12.3)].

5.3 Ototoxicity

Cases of tinnitus and reversible or irreversible hearing impairment and deafness have been reported with furosemide. Reports usually indicate that furosemide ototoxicity is associated with rapid injection, severe renal impairment, the use of higher than recommended doses, hypoproteinemia or concomitant therapy with aminoglycoside antibiotics, ethacrynic acid, or other ototoxic drugs. If the physician elects to use high-dose parenteral therapy, controlled intravenous infusion is advisable (for adults, an infusion rate not exceeding 4 mg furosemide per minute has been used) [see Drug Interactions (7)].

5.4 Acute Urinary Retention

In patients with severe symptoms of urinary retention (because of bladder emptying disorders, prostatic hyperplasia, urethral narrowing), the administration of furosemide can cause acute urinary retention related to increased production and retention of urine. These patients require careful monitoring, especially during the initial stages of treatment.

5.5 Incomplete Dosing

The Lasix ONYU Infusor should not come in contact with water or any other fluids (blood or drug product). Fluid contact with the Infusor circuit board can lead to device errors and premature termination of infusion.
The Lasix ONYU is intended for use in a setting where the patient can limit their activity for the duration of administration. Certain patient movements may cause interruption of device adherence to skin and premature termination of infusion.
Lasix ONYU should only be used in patients who can detect and respond to alarms to ensure a complete dose is administered.

6 ADVERSE REACTIONS

The following important adverse reactions are discussed elsewhere in the labeling:

- Fluid, Electrolyte, and Metabolic Abnormalities [see Warnings and Precautions (5.1)].
- Ototoxicity [see Warnings and Precautions (5.3)]

The following adverse reactions associated with the use of furosemide were identified in clinical trials or post-marketing reports. Because these reactions were reported voluntarily from a population of uncertain size, it is not always possible to estimate their frequency reliably, or to establish a causal relationship to drug exposure.

Adverse reactions are categorized below by organ system and listed by decreasing severity.

Gastrointestinal System Reactions: pancreatitis, jaundice (intrahepatic cholestatic jaundice), increased liver enzymes, anorexia, oral and gastric irritation, cramping, diarrhea, constipation, nausea, vomiting.

Systemic Hypersensitivity Reactions: severe anaphylactic or anaphylactoid reactions (e.g., with shock), systemic vasculitis, interstitial nephritis, necrotizing angiitis.

Central Nervous System Reactions: tinnitus and hearing loss, paresthesias, vertigo, dizziness, headache, blurred vision, xanthopsia.

Hematologic Reactions: aplastic anemia, thrombocytopenia, agranulocytosis, hemolytic anemia, leukopenia, anemia, eosinophilia.

Dermatologic Hypersensitivity Reactions: toxic epidermal necrolysis, Stevens-Johnson Syndrome, erythema multiforme, drug rash with eosinophilia and systemic symptoms, acute generalized exanthematous pustulosis, exfoliative dermatitis, bullous pemphigoid, purpura, photosensitivity, rash.

Cardiovascular Reactions: orthostatic hypotension, increase in cholesterol and triglyceride serum levels.

Administration Site and Skin Reactions: erythema, bruising, edema, infusion site pain.

Other Reactions: glycosuria, muscle spasm, weakness, restlessness, urinary bladder spasm, thrombophlebitis, transient injection site pain following intramuscular injection, fever.

7 DRUG INTERACTIONS

7.1 Effects of Furosemide on Other Drugs

Table 1: Effects of Furosemide on Other Drugs
Drug/Substance Class or Name | Drug Interaction Effect | Recommendations
Aminoglycoside antibiotics | Furosemide may increase the ototoxic potential of aminoglycoside antibiotics, especially in the presence of impaired renal function [see Warnings and Precautions (5.3)]. | Avoid combination except in life-threatening situations.
Ethacrynic acid | Possibility of ototoxicity [see Warnings and Precautions (5.3)]. | Avoid concomitant use with ethacrynic acid.
Salicylates | May experience salicylate toxicity at lower doses because of competitive renal excretory sites. | Monitor for symptoms of salicylate toxicity.
Cisplatin Cisplatin and nephrotoxic drugs | There is a risk of ototoxic effects if cisplatin and furosemide are given concomitantly [see Warnings and Precautions (5.3)]. Nephrotoxicity | Administer furosemide at lower doses and with positive fluid balance when used to achieve forced diuresis during cisplatin treatment. Monitor renal function.
Paralytic agents | Furosemide has a tendency to antagonize the skeletal muscle relaxing effect of tubocurarine and may potentiate the action of succinylcholine. | Monitor for skeletal muscle effect.
Lithium | Furosemide reduces lithium’s renal clearance and adds a high-risk of lithium toxicity. | Avoid concomitant use with lithium.
Angiotensin converting enzyme inhibitors or angiotensin II receptor blockers | May lead to severe hypotension and deterioration in renal function, including renal failure. | Monitor for changes in blood pressure and renal function and interrupt or reduce the dosage of furosemide, angiotensin converting enzyme inhibitors, or angiotensin receptor blockers if needed.
Antihypertensive drugs | Furosemide may add to or potentiate the therapeutic effect of other antihypertensive drugs. | Monitor for changes in blood pressure and adjust the dose of other antihypertensive drugs if needed.
Adrenergic blocking drugs or peripheral adrenergic blocking drugs | Potentiation occurs. | Monitor for changes in blood pressure and adjust the dose of adrenergic blocking drugs if needed.
Norepinephrine | Furosemide may decrease arterial responsiveness (vasoconstricting effect) to norepinephrine. | Monitor blood pressure (or mean arterial pressure).
Chloral hydrate | In isolated cases, intravenous administration of furosemide within 24 hours of taking chloral hydrate may lead to flushing, sweating attacks, restlessness, nausea, increase in blood pressure, and tachycardia. | Concomitant use with chloral hydrate is not recommended.
Methotrexate and other drugs undergoing renal tubular secretion | Furosemide may decrease renal elimination of other drugs that undergo tubular secretion. High-dose treatment of furosemide may result in elevated serum levels of these drugs and may potentiate their toxicity. | Monitor serum levels of drugs undergoing renal tubular secretion and adjust the dose if needed.
Cephalosporin | Furosemide can increase the risk of cephalosporin-induced nephrotoxicity even in the setting of minor or transient renal impairment. | Monitor for changes in renal function.
Cyclosporine | Increased risk of gouty arthritis secondary to furosemide-induced hyperuricemia and cyclosporine impairment of renal urate excretion. | Monitor serum urate levels.
Thyroid hormones | High doses (> 80 mg) of furosemide may inhibit the binding of thyroid hormones to carrier proteins and result in transient increase in free thyroid hormones, followed by an overall decrease in total thyroid hormone levels. | Monitor the total thyroid hormone levels.

7.2 Effect of Other Drugs on Furosemide

Table 2: Effect of Other Drugs on Furosemide
Drug/Substance Class or Name | Drug Interaction Effect | Recommendations
Phenytoin | Phenytoin interferes directly with renal action of furosemide. | Monitor diuretic effects of furosemide and adjust the dose of furosemide if needed.
Methotrexate and other drugs undergoing renal tubular secretion | May reduce the effect of furosemide. High-dose treatment of methotrexate and these other drugs may result in elevated serum levels of furosemide and may potentiate the toxicity of furosemide. | Monitor for enhanced toxicity of furosemide.
Indomethacin | Coadministration of indomethacin may reduce the natriuretic and antihypertensive effects of furosemide in some patients by inhibiting prostaglandin synthesis. Indomethacin may also affect plasma renin levels, aldosterone excretion, and renin profile evaluation. | Patients receiving both indomethacin and furosemide should be observed closely to determine if the desired diuretic and/or antihypertensive effect of furosemide is achieved.

8 USE IN SPECIFIC POPULATIONS

8.1 Pregnancy

Risk Summary

Available data from published observational studies, case reports, and post marketing reports, from decades of use, have not demonstrated a drug-associated risk of major birth defects, miscarriage, or other adverse maternal or fetal outcomes with furosemide use during pregnancy. Untreated congestive heart failure can lead to adverse outcomes for the mother and the fetus (see Clinical Considerations).

In animal reproduction studies, furosemide has been shown to cause unexplained maternal deaths and abortions in rabbits when administered orally during organogenesis at 4 times a human i.v. dose of 80 mg based on body surface area (BSA) and oral bioavailability corrections, presumably secondary to volume depletion (see Data).

The background risk for major birth defects and miscarriage for the indicated populations is unknown. All pregnancies have a background risk of birth defect, loss, or other adverse outcomes. In the U.S. general population, the estimated background risk of major birth defects and miscarriage in the clinically recognized pregnancies is 2% to 4% and 15% to 20%, respectively.

Clinical Considerations

Disease-associated Maternal and/or Embryo/fetal Risk

Pregnant women with congestive heart failure are at increased risk for pre-term birth. Stroke volume and heart rate increase during pregnancy, increasing cardiac output, especially during the first trimester.

Clinical classification of heart disease may worsen with pregnancy and lead to maternal death and/or stillbirth. Closely monitor pregnant patients for destabilization of their heart failure.

Data

Animal Data

The effects of furosemide on embryonic and fetal development and on pregnant dams were studied in mice, rats, and rabbits.

Furosemide caused unexplained maternal deaths and abortions in rabbits at the lowest dose of 25 mg/kg (approximately 4 times the human i.v. dose of 80 mg based on BSA and oral bioavailability corrections). In another study, a dose of 50 mg/kg (approximately 7 times a human i.v. dose of 80 mg based on BSA and oral bioavailability corrections) also caused maternal deaths and abortions when administered to rabbits between Days 12 and 17 of gestation. In a third study, none of the pregnant rabbits survived an oral dose of 100 mg/kg. Data from the above studies indicate fetal lethality that can precede maternal deaths.

The results of the mouse study and one of the three rabbit studies also showed an increased incidence and severity of hydronephrosis (distention of the renal pelvis and, in some cases, of the ureters) in fetuses of treated dams as compared with the incidence of fetuses from the control group.

8.2 Lactation

Risk Summary

The presence of furosemide has been reported in human breast milk. There are no data on the effects on the breastfed infant or the effects on milk production. Doses of furosemide associated with clinically significant diuresis may impair milk production. The developmental and health benefits of breastfeeding should be considered along with the mother’s clinical need for furosemide and any potential adverse effects on the breastfed infant from furosemide or from the underlying maternal condition.

8.4 Pediatric Use

Safety and efficacy for pediatric use have not been established [see Indications and Usage (1)].

8.5 Geriatric Use

Controlled clinical studies did not include sufficient numbers of subjects to determine whether subjects aged 65 and over respond differently from younger subjects. Other reported clinical experience has not identified differences in responses between the elderly and younger patients. In general, dose selection for the elderly patients should be cautious, reflecting the greater frequency of decreased hepatic, renal or cardiac function, and of concomitant disease or other drug therapy.

Lasix ONYU is known to be substantially excreted by the kidney, and the risk of toxic reactions to this drug may be greater in patients with impaired renal function. Because elderly patients are more likely to have decreased renal function, care should be taken in dose selection, and it may be useful to monitor renal function [see Clinical Pharmacology (12.3)].

8.6 Renal Impairment

Significantly reduced renal function can affect the response to furosemide. Lasix ONYU will deliver only an 80 mg dose of furosemide, and patients with significantly reduced renal function may require additional diuretic therapy.

8.7 Hepatic Impairment

In patients with hepatic cirrhosis and ascites, sudden alterations of fluid and electrolyte balance may precipitate hepatic encephalopathy and coma. Treat such patients in a setting where clinical status and electrolyte balance can be carefully monitored.

10 OVERDOSAGE

The principal signs and symptoms of overdose with Lasix ONYU are dehydration, blood volume reduction, hypotension, electrolyte imbalance, hypokalemia, and hypochloremic alkalosis, and are extensions of its diuretic action.

The concentration of furosemide in biological fluids associated with toxicity or death is not known.

Treatment of overdosage is supportive and consists of replacement of excessive fluid and electrolyte losses. Serum electrolytes, carbon dioxide level, and blood pressure should be determined frequently. Adequate drainage must be assured in patients with urinary bladder outlet obstruction (such as prostatic hypertrophy).

Hemodialysis does not accelerate furosemide elimination.

11 DESCRIPTION

Lasix ONYU (furosemide injection) for subcutaneous use is a loop diuretic. Chemically, it is 4-chloro-N-furfuryl-5-sulfamoylanthranilic acid.

Furosemide is a white to slightly yellow crystalline powder. It is sparingly soluble in alcohol, freely soluble in dilute alkali solutions, and insoluble in dilute acids. The structural formula is as follows:

Molecular Formula: C12H11ClN2O5S

Molecular Weight: 330.75 g/mol

Lasix ONYU is a single-dose prefilled cartridge co-packaged with a single-use Disposable Unit of the Infusor.

The single-dose prefilled cartridge contains 80 mg furosemide in a 2.67 mL sterile, clear to slightly yellow, and nonpyrogenic aqueous solution. The pH of Lasix ONYU, 7.5, differs from that of Furosemide Injection, USP. Each 1 mL dose of Lasix ONYU contains 30 mg of furosemide and the following inactive ingredients: betadex sulfobutyl ether sodium (300 mg), hydrochloric acid for pH adjustment if needed, sodium hydroxide for pH adjustment if needed, tromethamine (3 mg), and water for injection (q.s.).

Each single-dose of Lasix ONYU is administered via an electromechanical (battery powered, microprocessor controlled) Infusor, pre-programmed to deliver 80 mg of Lasix ONYU over 5-hours using a bi-phasic delivery profile. The Infusor consists of a custom Reusable Unit which can be used for close to 50 treatments. The Reusable Unit is used with a Disposable Unit and single-dose prefilled cartridge which are provided together for the user as a Lasix ONYU Kit. The Disposable Unit must be discarded after use.

12 CLINICAL PHARMACOLOGY

12.1 Mechanism of Action

Furosemide primarily inhibits the reabsorption of sodium and chloride in the proximal and distal tubules and in the loop of Henle. The high degree of diuresis is largely due to the unique site of action. The action on the distal tubule is independent of any inhibitory effect on carbonic anhydrase and aldosterone.

12.2 Pharmacodynamics

In patients with NYHA Class II and Class III heart failure, subcutaneous administration of Lasix ONYU (30 mg furosemide over the first hour followed by 12.5 mg per hour for the subsequent 4 hours, total 80 mg furosemide within 5 hours) produced similar diuresis and natriuresis to intravenous administration (single 80 mg bolus) at 8- and 24-hour post-dose. The duration of diuretic effect with Lasix ONYU is at least 8 hours after initiation of dosing.

12.3 Pharmacokinetics

Absorption

In patients with NYHA Class II and Class III heart failure, subcutaneous infusion of Lasix ONYU (30 mg furosemide over the first hour followed by 12.5 mg per hour for the subsequent 4 hours, 80 mg furosemide total), the bioavailability was 112% (90% CI: 104, 120%), with a median Tmax of 5 hours relative to 80 mg intravenous furosemide (single 80 mg bolus). The pharmacokinetic parameters of Lasix ONYU are presented in Table 3 below:

Table 3: Pharmacokinetic Data of Lasix ONYU Following Subcutaneous Infusion (n = 18)
Dose | C max; (ng/mL) [Mean ± SD] | AUC t (ng×hr/mL) | T1/2 (hr) | AUC ∞; (ng×hr/mL)
Lasix ONYU: 30 mg subcutaneously infused over the first hour followed by 12.5 mg per hour for the subsequent 4 hours (total dose: 80 mg furosemide) | 2010 ± 391 | 13000 ± 2510 | 3.7 ± 0.7 | 13100 ± 2550
Furosemide administered as single 80 mg bolus dose intravenously | 13800 ± 4100 | 11900 ± 3380 | 3.7 ± 1.3 | 12000 ± 3400

The terminal half-life of furosemide is approximately 2 hours.

The impact of subcutaneous edema at the administration site of Lasix ONYU on drug absorption is unknown.

Distribution

Furosemide is extensively bound to plasma proteins, mainly to albumin. Plasma concentrations ranging from 1 mcg per mL to 400 mcg per mL are 91% to 99% bound in healthy individuals. The unbound fraction averages 2.3% to 4.1% at therapeutic concentrations.
Furosemide binding to albumin may be reduced in elderly patients.

Elimination

Significantly more furosemide is excreted in urine following the intravenous injection than after the tablet or oral solution.

Furosemide is predominantly excreted unchanged in the urine.

The renal clearance of furosemide after intravenous administration in older healthy male subjects (60 to 70 years of age) is significantly less than in younger healthy male subjects (20 to 35 years of age).

Metabolism

Furosemide glucuronide is the only or at least the major biotransformation product of furosemide in humans.

13 NONCLINICAL TOXICOLOGY

13.1 Carcinogenesis, Mutagenesis, Impairment of Fertility

Carcinogenesis

Furosemide was tested for carcinogenicity by oral administration in one strain of mice and one strain of rats. A small but significantly increased incidence of mammary gland carcinomas occurred in female mice at a dose approximately 8 times a human i.v. dose of 80 mg based on BSA and oral bioavailability corrections. There were marginal increases in uncommon tumors in male rats at a dose of 15 mg per kg (slightly greater than the maximum human dose) but not at 30 mg per kg.

Mutagenesis

Furosemide was devoid of mutagenic activity in various strains of Salmonella typhimurium when tested in the presence or absence of an in vitro metabolic activation system, and questionably positive for gene mutation in mouse lymphoma cells in the presence of rat liver S9 at the highest dose tested. Furosemide did not induce sister chromatid exchange in human cells in vitro, but other studies on chromosomal aberrations in human cells in vitro gave conflicting results. In Chinese hamster cells it induced chromosomal damage but was questionably positive for sister chromatid exchange. Studies on the induction by furosemide of chromosomal aberrations in mice were inconclusive. The urine of rats treated with this drug did not induce gene conversion in Saccharomyces cerevisiae.

Impairment of Fertility

Furosemide produced no impairment of fertility in male or female rats, at 100 mg per kg per day (the maximum effective diuretic dose in the rat), approximately 7 times a human i.v. dose of 80 mg based on BSA and oral bioavailability corrections.

16 HOW SUPPLIED/STORAGE AND HANDLING

Lasix ONYU injection is a sterile, clear to slightly yellow, non-pyrogenic liquid supplied in a single-dose prefilled cartridge for subcutaneous infusion co-packaged with a Disposable Unit. The Infusor with single-dose prefilled cartridge is designed to deliver 80 mg of Lasix ONYU in 2.67 mL solution over 5 hours.

Lasix ONYU Kit: Carton containing one 80 mg/2.67 mL single-dose prefilled cartridge co-packaged with a Disposable Unit and two alcohol pads. | NDC 81137‐001‐15
Starter Kit: Carton containing three Lasix ONYU Kits co-packaged with one Reusable Unit and one wall charger. | NDC 81137‐001‐35

Store between 20°C and 25°C (68°F and 77°F); excursions permitted between 15°C and 30°C (59°F and 86°F) [See USP Controlled Room Temperature]. Do not refrigerate or freeze.

Protect Lasix ONYU from light. Do not remove the prefilled cartridge from carton until it is ready for use. Do not use if the solution is discolored or cloudy. Protect the Infusor from water.

17 PATIENT COUNSELING INFORMATION

Advise the patient and/or caregiver to read the FDA-approved patient labeling [Instructions for Use].

Advise the patient that Lasix ONYU should not come into contact with water or other fluids. Patients should check the device for alarms to ensure a complete dose is administered [see Warnings and Precautions (5.5)].

Fluid, Electrolyte, and Metabolic Abnormalities

Advise patients that they may experience symptoms from excessive fluid and/or electrolyte losses. The postural hypotension that sometimes occurs can usually be managed by getting up slowly. Potassium supplements and/or dietary measures may be needed to control or avoid hypokalemia [see Warnings and Precautions (5.1)].

Advise patients that furosemide may increase blood glucose levels and thereby affect urine glucose tests [see Warnings and Precautions (5.1)].

Photosensitivity

The skin of some patients may be more sensitive to the effects of sunlight while taking furosemide [see Adverse Reactions (6)].

For more information about Lasix® ONYU, go to www.Lasix-ONYU.com or call 1-855-452-7496 (1-855-4LASIX6).

Lasix® ONYU (furosemide injection 80 mg/2.67 mL) for subcutaneous use

Manufactured for:
SQ Innovation, Inc.
20 Burlington Mall Road, Suite 220
Burlington, MA 01803
USA

Patent Protected
©2023

SQ Innovation Instructions for Use Lasix® ONYU (lay-six on-yoo) (furosemide injection) 80 mg/2.67 mL (30 mg/mL) for Subcutaneous Use with Infusor

These Instructions for Use contains information on how to use Lasix ONYU with the Infusor.

Contact Information:
SQ Innovation, Inc.
Burlington, MA 01803, USA
Phone: 1-855-452-7496 (1-855-4LASIX6)
www.Lasix-ONYU.com

1: Important Information You Need to Know

Before Using the Lasix ONYU Infusor

- Keep the Lasix ONYU Infusor out of sight and reach of children.
- The Lasix ONYU treatment is for adult patients only as prescribed by a healthcare provider.
- For subcutaneous (under the skin) use only. The Lasix ONYU Infusor delivers the medicine just under the skin.
- Use on the stomach only. Do not use on any other area of the body.
- The Lasix ONYU Infusor is intended to be used by a single person and should not be shared.
- Do not use the Prefilled Cartridge if the solution is cloudy, yellow-brown or contains floating particles. It should be clear or light yellow. If it is not clear or light yellow, contact your healthcare provider to get a new one.
- Do not use any part of the Lasix ONYU Infusor if it has expired. If it is expired, contact your healthcare provider to get a new one.
- Do not use any part of the Lasix ONYU Infusor (Prefilled Cartridge, Disposable Unit, Reusable Unit or Charger) if it appears to be broken or damaged or does not work right. Use a new one or call SQ Innovation at 1-855-452-7496.
- Do not use a Disposable Unit if it was dropped as it may be damaged or contaminated. Use a new one.
- Do not use the Lasix ONYU Infusor if you can see the needle. Do not touch the needle or put the Lasix ONYU Infusor on your stomach, as you may get an injury. Go to Troubleshooting: You Can See the Needle for instructions on what to do.
- Do not use more than 1 Lasix ONYU Infusor at a time.
- Do not do more than 2 infusions in a 24-hour period.
- Do not use a Disposable Unit or Prefilled Cartridge more than 1 time.

Before Starting a Treatment

- Talk with your healthcare provider before using the Lasix ONYU Infusor.
  Do not start an infusion unless directed to do so by your healthcare provider.
- A healthcare provider should train you before using the Lasix ONYU Infusor by yourself.
- Read the step-by-step instructions (go to Chapter 2: How to Use the Lasix ONYU Infusor) before using the Lasix ONYU Infusor by yourself.
- You may watch the optional training video.

During a Treatment

- Start the infusion within 7 hours of preparing the Lasix ONYU Infusor.
- The infusion will last about 5 hours. During this time, you should limit your activities so that your bending movements are limited. Wearing the Lasix ONYU Infusor while riding in a car or airplane is not recommended. Be sure you have access to a bathroom after starting the infusion. You should urinate (pee) a lot and will need to make frequent bathroom visits.
- Frequent urination is to be expected during use of the Lasix ONYU Infusor. Be sure you have access to a bathroom for up to 8 hours after starting the infusion.
- Call your healthcare provider if you did not urinate a lot (at least 2 times during the 5-hour infusion).
- Do not apply lotions, oils, or ointments to the stomach area where you will apply the Lasix ONYU Infusor.
- Do not get the Lasix ONYU Infusor wet. Doing so may damage the Lasix ONYU Infusor. Do not shower, bathe, or swim while wearing the Lasix ONYU Infusor.
- Do not remove the Lasix ONYU Infusor from the stomach until the infusion is done. Removing the Lasix ONYU Infusor before stopping it will expose the needle, and may injure you or others. Go to How to Stop the Lasix ONYU Infusor Early if you need to stop the infusion early.
- Do not use the Lasix ONYU Infusor in or around a Magnetic Resonance Imaging (MRI) machine.
- Do not use the Lasix ONYU Infusor within 12 inches of mobile phones, tablets, computers, or wireless accessories (for example: TV remote control, Bluetooth computer keyboard or mouse) during the 5-hour infusion. It may cause the Lasix ONYU Infusor to break.

2: How to Use the Lasix ONYU Infusor

Inside the Box

Contents of the Lasix ONYU Kit

Note: The Single-Dose Prefilled Cartridge is referred to as Prefilled Cartridge throughout this Instructions for Use.

Contents of the Reusable Unit and Charger Box

Contents of the Lasix ONYU Starter Kit

Supplies not included:

- Cotton ball and small adhesive bandage (if needed) for Step 21 in End the Infusion.
- You will also need a sharps disposal container for Step 25 in Throw Away (Disposal), Cleaning, and Storage. You may obtain a free sharps disposal container from SQ Innovation. Visit www.Lasix-ONYU.com/sharps/ or call 1-855-452-7496 to have a container mailed
  to you at no charge.

Get to Know the Lasix ONYU Infusor Parts

Get Ready for the Infusion

Do not start an infusion unless directed to do so by your healthcare provider.

Step 1

Gather the white Reusable Unit, Charger, and 1 Lasix ONYU Kit.

Only use the Charger that has been provided.

Do not use if the Disposable Unit was dropped or if any parts appear to be broken or damaged. Use a new one.

Step 2

Charge the Reusable Unit. Plug the Charger into the back of the white Reusable Unit and a power outlet. Check the Battery Light:

- When the Battery Light turns solid blue, unplug the charger from the Reusable Unit. The Reusable Unit is ready to use.
- If the Battery Light is flashing blue, wait for charging to finish.
- If any lights are red, unplug the Charger and plug it back in. If the lights are still red, go to Troubleshooting: Lights and Tones Table for instructions.
  Always charge the Reusable Unit before each infusion.

Prepare the Medicine

Step 3
Wash your hands with soap and water.

Step 4

Check the expiration date on the Lasix ONYU Kit.

Do not use if the expiration date has passed.

Step 5

Gather all supplies needed. On a clean, flat, well-lit work surface, open 1 Lasix ONYU Kit and remove the contents.

Do not open the contents until you are ready to start the infusion.

Do not use the Disposable Unit if the sealed packaging appears to be damaged. Use a new one.

Do not use the Disposable Unit if it was dropped or if any parts appear to be broken. Use a new one.

Step 6

Remove Prefilled Cartridge, Disposable Unit, and 2 alcohol pads from packaging:

- Remove the Prefilled Cartridge from its box and sealed tray.
- Remove the Disposable Unit from its sealed package.

Do not remove the paper liner from the back of the Disposable Unit.

Step 7

Check the Prefilled Cartridge appearance.

Do not use the Prefilled Cartridge if the medicine is cloudy, appears yellow-brown, or you see floating particles.

Step 8
Wipe the silver top of the Prefilled Cartridge with an alcohol pad.

Step 9

Push the Prefilled Cartridge into the green Disposable Unit with the silver top inserted first.

The Prefilled Cartridge is fully inserted when the bottom of the Prefilled Cartridge is at the tip
of the arrow on the Disposable Unit.

Prepare the Lasix ONYU Infusor

Step 10

Check the following:

- The Reusable Unit Battery Light is solid blue, and
- The Charger is disconnected from the Reusable Unit.
  Slide together the white Reusable Unit and green Disposable Unit together until the Status Light on the Reusable Unit turns on.

Step 11

Check the Status Light.

- If the Status Light is blue and flashing fast, and you hear the OK Tone (1 long beep), continue to Step 12. The Lasix ONYU Infusor is ready to start your infusion.
- The Lasix ONYU Infusor will remain ready to start infusion for 7 hours.
- If the Status Light is flashing red and you hear the Alarm Tone (2 short beeps), do not use the Lasix ONYU Infusor. Go to Troubleshooting: The Status Light is Flashing Red for instructions.
- If the Battery Light is solid red, do not use the Lasix ONYU Infusor. Go to Troubleshooting: Checking the Reusable Unit Battery for instructions.

Prepare the Application Site

Step 12

Choose a site on the stomach, above the beltline, to the left or right of the belly button.
Trim excessive hair at the site. This will help the Lasix ONYU Infusor stick to the skin.
Alternate (rotate) sites between left and right sides of the stomach with each infusion.

Do not choose a site where:

- the skin is irritated, broken, tender, red, bruised, or hard,
- the skin is wet or sweaty,
- there are folds in the skin when standing up straight, or
- belts, waistbands, or tight clothing may rub against or move the Lasix ONYU Infusor.

Step 13

Wipe the site with an alcohol pad.

Let dry for at least 10 seconds.

Attach the Lasix ONYU Infusor

Step 14

Hold the blue tab with one hand and use the other hand to peel off the paper liner from the adhesive on the back of the Lasix ONYU Infusor.

Leave the sticky adhesive on the Lasix ONYU Infusor. Only remove the paper liner.

Do not touch the sticky adhesive with your fingers or let it touch any surfaces before sticking the Lasix ONYU Infusor to your stomach.

Step 15

While standing up straight, press the Lasix ONYU Infusor onto the site on your stomach you wiped with the alcohol pad.

Make sure the Status Light and the Start/Stop Button are facing up in a horizontal position as shown, so you can see them when the Lasix ONYU Infusor is on your stomach.

Step 16

Rub the edges of the adhesive with a finger to get the Lasix ONYU Infusor to stick well.

Start the Infusion

Start your infusion within 7 hours of connecting the Reusable Unit and Disposable Unit. If more than 7 hours pass without starting your infusion, the Lasix ONYU Infusor will time out and the infusion cannot be delivered (go to Troubleshooting: The Status Light is Flashing Red).

Step 17

Press and hold the Start/Stop Button until you hear the motor and see the blue Status Light change to flashing slow.

The needle will automatically insert into your skin after the Start/Stop Button is pressed. You may feel a slight pinch.

You will hear the motor start and stop often during your infusion. The motor runs for a few seconds at a time then pauses for several minutes.

Step 18

Check the Status Light.

- If the Status Light is blue and flashing slow, and you hear the OK Tone (1 long beep), the infusion has started. You will hear the motor running.
- If the Status Light is flashing red, and you hear the Alarm Tone (2 short beeps), the infusion did not start. Go to Troubleshooting: The Status Light is Flashing Red for instructions.
- If the Status Light is blue and flashing fast, and you hear the OK Tone (1 long beep), the infusion did not start. Repeat Step 17.
- For additional assistance go to Troubleshooting: Lights and Tones Table for instructions or call 1-855-452-7496.

During the Infusion

Step 19

Wait 5 hours for the Lasix ONYU Infusor to deliver the full infusion.

You will see the blue Status Light flashing slow and sometimes hear the motor running.

Check the Lasix ONYU Infusor every now and then to make sure it is working properly.

Do not remove the Lasix ONYU Infusor from your stomach until the infusion is done. The infusion is complete when the Status Light is solid blue and you hear the OK Tone (1 long beep). Go to Troubleshooting: How to Stop the Infusor Early if you need to stop the infusion early.

End the Infusion

Step 20

After 5 hours, check the Status Light.

- If the Status Light is solid blue, and you hear the OK Tone (1 long beep), the infusion is done.
- If the Status Light is flashing red, and you hear the Alarm Tone (2 short beeps), an error happened. Go to Troubleshooting: The Status Light is Flashing Red.
- If the Status Light is blue and flashing slow, and you hear the OK Tone (1 long beep), the infusion is not done yet. Continue to wait.

The needle automatically pulls in (retracts) when the infusion is done. You may feel a slight pinch.

Step 21

When the infusion is done, remove the Lasix ONYU Infusor from your stomach. Peel the Lasix ONYU Infusor off the skin by holding down the skin and pulling the blue tab away from the stomach.

You might have some discomfort after you remove the Lasix ONYU Infusor. This discomfort should quickly go away, but some redness of the skin may remain. If there is any bleeding, pat with a small cotton ball or apply a small adhesive bandage over the site.

Confirm the Infusion Worked

Step 22

Look in the window on the back of the Infusor to check whether all the medicine was delivered.

- If the middle of the window is all gray (whole gray stopper is visible with very little or no liquid), all of the medicine was delivered.
  If you see anything else (like a lot of liquid, a large bubble in the liquid, no gray stopper, or only part of the gray stopper), some of the medicine was not delivered. Call your healthcare provider right away.

Step 23

Confirm the medicine worked.

- If you urinate a lot (at least 2 times during the 5-hour infusion), the medicine worked.
- If you urinate less than 2 times (during the 5-hour infusion), the medicine may not have worked. Call your healthcare provider right away.

Throw Away (Disposal), Cleaning, and Storage

Step 24

Pull apart the green Disposable Unit and white Reusable Unit.

The Reusable Unit automatically turns off when the two parts are separated.

Step 25

Do not save and re-use the green Disposable Unit or Prefilled Cartridge. They are for one-time use only.

Throw away the green Disposable Unit into an FDA-cleared sharps disposal container.

You may obtain a free sharps disposal container from SQ Innovation. Visit www.Lasix-ONYU.com/sharps/ or call 1-855-452-7496 to have a container mailed to you at no charge.

Alternatively, if you do not have an FDA-cleared sharps disposal container, you may use a household container that is:

- made of heavy-duty plastic,
- can be closed with a tight fitting, puncture-resistant lid, without sharps being able to come out,
- upright and stable during use,
- leak-resistant, and
- properly labeled to warn of hazardous waste inside the container.

When your Sharps container is almost full, you will need to follow your community guidelines for the right way to dispose of your sharps disposal container. There may be state or local laws about how you throw away used needles and syringes. For more information about safe sharps disposal and for specific information about sharps disposal in the state that you live in, go to the FDAs website at:

https://www.fda.gov/medical-devices/safely-using-sharps-needles-and-syringes-home-work-and-travel/best-way-get-rid-used-needles-and-other-sharps

Do not dispose of your used sharps disposal container in your household trash unless your community guidelines permit this.

Do not recycle the green Disposable Unit and used sharps disposal container or throw them away into household trash.

Important: Always keep the sharps disposal container out of the reach of children.

Scan the code below with your phone for a sharps disposal location near you or call Safe Needle Disposal at 1-800-643-1643.

Step 26

Wipe the white Reusable Unit with a clean, water-damp cloth to remove visible dirt right after use. Let dry completely before storing.

If needed, a mild detergent, like dish soap, may be added to the damp cleaning cloth.

Do not use harsh cleaners that contain bleach, alcohol, ammonia, or other solvents. These cleaners may damage the Reusable Unit.

Do not submerge the Reusable Unit in liquids or spray liquids directly on the surface. It contains parts that should not get wet.

Step 27

Store the Reusable Unit, Charger, and any remaining Lasix ONYU Kits for next use.

- Keep at room temperature between 68°F and 77°F (20°C and 25°C).
- Do not refrigerate or freeze.
- Keep in a dark place to protect from light.
- Keep dry.
- Keep extra Prefilled Cartridges and Disposable Units in their original packaging until it is time to use them.

INSTRUCTIONS FOR USE

3: Troubleshooting

Customer Service Contact Information

Contact Information:
SQ Innovation, Inc.
Burlington, MA 01803, USA
Phone: 1-855-452-7496 (1-855-4LASIX6)
www.Lasix-ONYU.com

Lights and Tones Table

Checking the Reusable Unit Battery

If the Battery Light is charged, the white Reusable Unit is able to deliver a full infusion. If the Battery Light is low, the Reusable Unit cannot deliver a full infusion and it needs to be charged.

Always charge the Reusable Unit before you use a new Disposable Unit (before each infusion).

Charging may take up to 20 minutes.

A. Battery Light is flashing blue

The Reusable Unit battery is being charged. Wait until the Battery Light turns solid blue before using the Lasix ONYU Infusor.

B. Battery Light is solid blue

The Reusable Unit battery is done charging and ready to use.

C. Battery Light is solid red before preparing the Lasix ONYU Infusor for use

The Reusable Unit battery is low and cannot deliver a full infusion.

Charge the Reusable Unit:

1. Plug the Charger into the back of the Reusable Unit.
2. Plug the other end of the Charger into a power outlet.
3. Wait until the Battery Light turns solid blue.

D. Battery Light is solid red when the Disposable Unit and Reusable Unit are connected

The Reusable Unit battery is low and the Lasix ONYU Infusor will not start.

1. Pull apart the white Reusable Unit and green Disposable Unit.
2. Put the Disposable Unit to the side while you charge the Reusable Unit (do not remove the Prefilled Cartridge from the Disposable Unit).
3. Charge the Reusable Unit:
  1. Plug the Charger into the back of the Reusable Unit.
  2. Plug the other end of the Charger into a power outlet.
  3. Wait until the Battery Light turns solid blue.
  4. Follow instructions beginning with Step 10 in Prepare the Lasix ONYU Infusor to connect the Reusable Unit to the Disposable Unit.

The Reusable Unit Has Expired

When the Reusable Unit expires, the Lasix ONYU Infusor can no longer be used. The Reusable Unit needs to be replaced.

The Reusable Unit is expired if it does not light up at all after charging or the Status Light and the Battery Light are both solid red when the Reusable Unit is plugged in or when the Reusable Unit and Disposable Unit are pulled apart.

Call 1-855-452-7496 for a replacement Reusable Unit, which will be shipped overnight when possible. Also call your healthcare provider.

The Reusable Unit should not be thrown away (disposed of) with household waste and should not be recycled in your local recycling program. Throw away the Reusable Unit according to local regulations for electronic devices with lithium batteries.

Alternatively, the Reusable Unit may be returned to SQ Innovation, free of charge, for proper and safe recycling. Go to Chapter 4 for more information.

The Status Light is Flashing Red

When an error happens inside the Lasix ONYU Infusor or the white Reusable Unit and green Disposable Unit have been connected for 7 hours without starting infusion, the Status Light will flash red and you will hear a repeating Alarm Tone (2 short beeps).

This can happen in the following 2 situations:

- Before the white Reusable Unit and green Disposable Unit are connected, see Section A below for what to do.
- After the white Reusable Unit and green Disposable Unit are connected, see Section B below for what to do.

A. If the Status Light flashes red before the white Reusable Unit is connected to the green Disposable Unit, a device error happened. Follow the instructions below:

1. Unplug the Charger (if it is connected).
2. Press and hold the Start/Stop Button until the flashing red light turns off (1 second).
3. Plug the charger into the Reusable Unit and a power outlet. Check the Lights:
  - If the Battery Light is solid or flashing blue, the Reusable Unit is ready to use. Continue with Step 2 in Get Ready for the Infusion.
  - If the Status Light is still flashing red, the Reusable Unit cannot be used. Call 1-855-452-7496 for a replacement Reusable Unit, which will be shipped overnight when possible. Also call your healthcare provider.

B. If the Status Light flashes red after connecting the white Reusable Unit and green Disposable Unit, a device error happened or the Lasix ONYU Infusor timed out (because it was connected for 7 hours without starting the infusion). The Lasix ONYU Infusor cannot be used. Follow the steps below:

1. If the Lasix ONYU Infusor is on the body, remove it from the stomach.
2. If you can see the needle, do not touch the needle because you could get an injury.
3. Pull apart the Reusable Unit and Disposable Unit.
4. Throw away the Disposable Unit with the Prefilled Cartridge into an FDA-cleared sharps disposal container (see Step 25 in Throw Away (Disposal), Cleaning, and Storage). You should not throw away the Disposable Unit in the household trash.
  - Do not save and re-use the Disposable Unit or Prefilled Cartridge as the medicine may be contaminated. They are for one-time use only.
5. Determine the next steps:
  1. If the error happened before the infusion was started, get a new Lasix ONYU Kit and start over at Step 1 in Get Ready for the Infusion.
  2. If the error happened after the infusion was started, call your healthcare provider to see what to do because some of the medicine was not delivered.

You Can See the Needle

You may see the needle in one of these situations:

- You press the Start/Stop Button before the Lasix ONYU Infusor is placed on the stomach, see Section A below for what to do.
- You remove the Infusor before infusion is done or the Lasix ONYU Infusor falls off during the 5-hour infusion, see Section B below for what to do.
- The needle did not retract automatically after infusion, see Section C below for what to do.

Do not touch the needle because you could get an injury.

A. If you see the needle before the Lasix ONYU Infusor is placed on the stomach, you should start over with a new Lasix ONYU Kit. Follow the steps below:

1. Press and hold the Start/Stop Button (4 seconds) until the Status Light flashes red and you hear the Alarm Tone (2 short beeps).
2. Pull apart the white Reusable Unit and green Disposable Unit.
3. Throw away the Disposable Unit with Prefilled Cartridge into an FDA-cleared sharps disposal container. You should not throw away the Disposable Unit in the household trash.
  - Do not save and re-use the Disposable Unit or Prefilled Cartridge as the medicine may be contaminated. They are for one-time use only.
4. Return to Step 1 in Get Ready for the Infusion to start over with a new Lasix ONYU Kit. Be careful not to press the Start/Stop Button until after the Lasix ONYU Infusor is on the stomach.

B. If you see the needle because the Lasix ONYU Infusor fell off or it was removed before infusion was done, follow the steps below:

You should not stick the Infusor back on the stomach because it may fall off again.

1. Press and hold the Start/Stop Button (4 seconds) until the Status Light flashes red and you hear the Alarm Tone (2 short beeps).
2. Pull apart the white Reusable Unit and green Disposable Unit.
3. Throw away the Disposable Unit with the Prefilled Cartridge into an FDA-cleared sharps disposal container. You should not throw away the Disposable Unit in the household trash.
  - Do not save and re-use the Disposable Unit or Prefilled Cartridge as the medicine may be contaminated. They are for one-time use only.
4. Call your healthcare provider to see what to do because some of the medicine was not delivered.

C. If you see the needle after the 5-hour infusion is done, the needle did not retract automatically. Follow the steps below:

1. Carefully pull apart the white Reusable Unit and green Disposable Unit.
2. Throw away the Disposable Unit with the Prefilled Cartridge into an FDA-cleared sharps disposal container. You should not throw away the Disposable Unit in the household trash.
  - Do not save and re-use the Disposable Unit or Prefilled Cartridge as the medicine may be contaminated. They are for one-time use only.
3. Continue with Step 26 and Step 27 in Throw Away (Disposal), Cleaning, and Storage to clean and store the Reusable Unit.

How to Stop the Lasix ONYU Infusor Early

Follow these steps below if you need to stop the Lasix ONYU Infusor before the 5-hour infusion is finished. Do not remove the Lasix ONYU Infusor from the stomach before stopping it. Removing the Lasix ONYU Infusor from the body before stopping it will expose the needle, and you could get an injury if you touch it.

1. Press and hold the Start/Stop Button (4 seconds) until you hear the Alarm Tone (2 short beeps) and the Status Light is flashing red.
2. Confirm infusion was stopped. Check the Status Light:
  - If the Status Light is flashing red and you hear the Alarm Tone (2 short beeps), infusion has stopped. The needle will retract shortly after you press the Start/Stop Button.
  - If the Status Light is blue and flashing slow, the infusion did not stop. Repeat Step 1 in How to Stop the Lasix ONYU Infusor Early above.
3. The infusion cannot be restarted. You must remove the Lasix ONYU Infusor and contact your healthcare provider. Follow the steps below:
  1. Remove the Lasix ONYU Infusor from your stomach.
  2. Pull apart the white Reusable Unit and green Disposable Unit.
  3. Throw away the Disposable Unit withthe Prefilled Cartridge in an FDA-cleared sharps disposal container. You should not throw away the Disposable Unit in the household trash.
  - Do not save and re-use the Disposable Unit or Prefilled Cartridge as the medicine may be contaminated. They are for one-time use only.
  - Call your healthcare provider because you did not get all of the medicine.

You Did Not Urinate (Pee) Much During Infusion

The Lasix ONYU Infusor delivers a diuretic medicine which should make you urinate a lot. If you do not urinate a lot (at least 2 times during the 5-hour infusion), there are two reasons this could have happened:

- The diuretic medicine, Lasix ONYU, was not effective for you, or
- The Lasix ONYU Infusor did not work properly.

In either case, it is important that you call your healthcare provider. Follow the steps below to determine whether the Lasix ONYU Infusor worked and if all the medicine was delivered:

1. Remove the Lasix ONYU Infusor from your stomach.
2. Look at the window on the back of the Lasix ONYU Infusor:
  - If the middle of the window is all gray (whole gray stopper is visible with very little or no liquid), all the medicine was delivered. The Lasix ONYU Infusor worked.
  - If you see anything else (like a lot of liquid, a large bubble in the liquid, no gray stopper, or only part of the gray stopper), some of the medicine was not delivered. You did not get a full infusion.
3. Check your stomach: If you see or feel a lot of liquid on your stomach, you may not have received a full infusion due to the medicine leaking.

The Reusable Unit Does Not Light Up

This can happen in the following situations:

- The Reusable Unit has not been used for a long time or the Reusable Unit is expired, see Section A below for what to do.
- The Reusable Unit and Disposable Unit have been connected for more than 7 hours and infusion has not been started, see Section B below for what to do.

A. If the white Reusable Unit does not light up, try charging it, even if it has recently been charged. The Battery Light on the Reusable Unit must always be solid blue before connecting it to the Disposable Unit.

Follow the steps below:

1. Plug the Charger into the back of the Reusable Unit and plug the other end of the Charger into a power outlet.
2. Wait 20 minutes.
3. Disconnect the Charger from the Reusable Unit and power outlet.
4. Check the Battery Light:
  - If the Battery Light is solid blue, the Reusable Unit is ready to use.
  - If the Battery Light did not light up after 20 minutes of charging, the Reusable Unit expired. Call 1-855-452-7496 for a replacement Reusable Unit, which will be shipped overnight when possible. Also call your healthcare provider. Go to Troubleshooting: The Reusable Unit Has Expired for more information.
  - If you see other lights, go to Troubleshooting: Lights and Tones Table.

B. If the Reusable Unit and Disposable Unit have been connected for more than 7 hours and infusion has not been started, the Lasix ONYU Infusor will automatically time out. The Lasix ONYU Infusor cannot be restarted.

Follow the steps below:

1. If the Lasix ONYU Infusor is on the body, remove the Lasix ONYU Infusor from your stomach.
2. If you can see the needle, do not touch the needle because you could get an injury.
3. Pull apart the Reusable Unit and Disposable Unit.
4. Throw away the Disposable Unit with the Prefilled Cartridge in an FDA-cleared sharps disposal container. You should not throw away the Disposable Unit in the household trash.
  - Do not save and re-use the Disposable Unit or Prefilled Cartridge as the medicine may be contaminated. They are for one-time use only.
5. Get a new Lasix ONYU Kit and start over at Step 1 in Get Ready for the Infusion.

The Lasix ONYU Infusor Will Not Start the Infusion

You press the Start/Stop Button and the infusion does not start.

This can happen in the following situations:

- The Reusable Unit and Disposable Unit are not properly connected, see Section A below for what to do.
- The Reusable Unit is powered off and both the Battery Light and Status Light are off, go to Troubleshooting: The Reusable Unit Does Not Light Up for what to do.
- A device error has happened and the Status Light is flashing red, go to Troubleshooting: The Status Light is Flashing Red for what to do.

A. If the infusion does not start, follow the steps below:

1. Firmly push the Reusable Unit and Disposable Unit together. There should be no gap or space between the parts when they are properly connected.
2. Check the Status Light:
  - If the Status Light is blue and flashing fast and you hear the OK Tone (1 long beep), the Lasix ONYU Infusor is properly connected. The Lasix ONYU Infusor is ready to deliver infusion.
    If the Lasix ONYU Infusor is not on the body, go to Step 12 in Prepare the Application site.
    If the Lasix ONYU Infusor is on the body, go to Step 17 in Start the infusion.
  - If the Status Light is flashing red and you hear the Alarm Tone (2 short beeps), there is a problem with the Infusor. Go to Troubleshooting: The Status Light is Flashing Red to see what to do.

This Instructions for Use has been approved by the U.S. Food and Drug Administration.

Issued: 10/2025

SP110004US

Symbols

Treatment Kit Label Artwork

Starter Kit Label Artwork